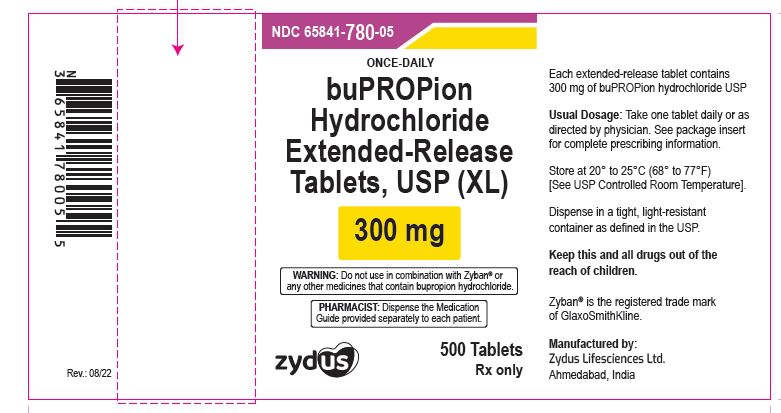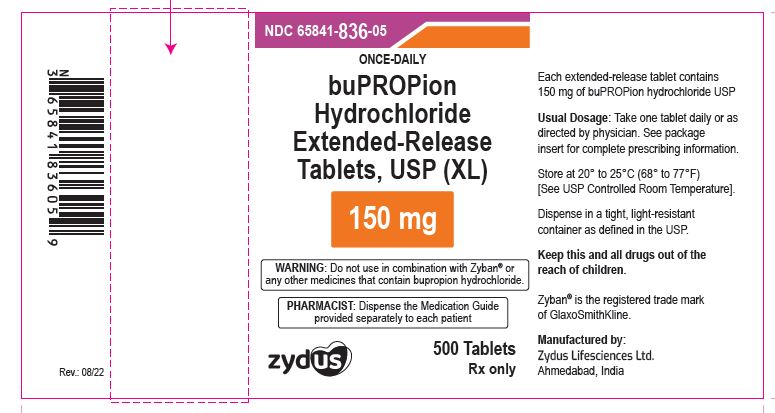 DRUG LABEL: bupropion
NDC: 65841-780 | Form: TABLET, EXTENDED RELEASE
Manufacturer: Zydus Lifesciences Limited
Category: prescription | Type: HUMAN PRESCRIPTION DRUG LABEL
Date: 20241126

ACTIVE INGREDIENTS: BUPROPION HYDROCHLORIDE 300 mg/1 1
INACTIVE INGREDIENTS: HYPROMELLOSES; MAGNESIUM STEARATE; METHACRYLIC ACID; POLYETHYLENE GLYCOL, UNSPECIFIED; TRIETHYL CITRATE; POVIDONE; ETHYLCELLULOSES; SILICON DIOXIDE; BUTYL ALCOHOL; FERROSOFERRIC OXIDE; ISOPROPYL ALCOHOL; PROPYLENE GLYCOL; SHELLAC; AMMONIA

BUPROPION HYDROCHLORIDE EXTENDED-RELEASE TABLETS (XL)

MEDICATION GUIDE

Manufactured by:

Cadila Healthcare Ltd.

India.

PACKAGE LABEL.PRINCIPAL DISPLAY PANEL

NDC 65841-780-05

Bupropion Hydrochloride Extended-release Tablets USP (XL), 300 mg

500 Tablets

Rx only

NDC 65841-836-05

Bupropion Hydrochloride Extended-release Tablets USP (XL), 150 mg

500 Tablets

Rx only